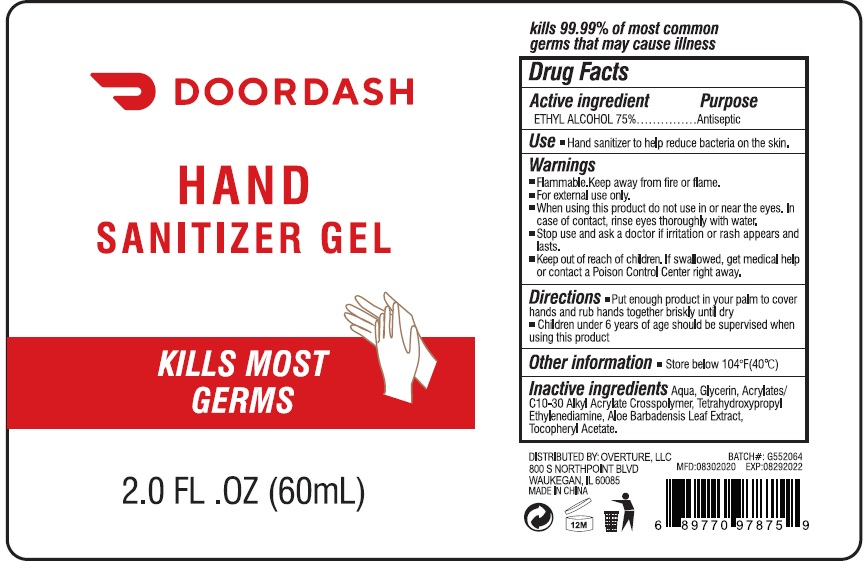 DRUG LABEL: Hand Sanitizer Gel
NDC: 74168-006 | Form: GEL
Manufacturer: ZHEJIANG YASILI COSMETICS CO.,LTD
Category: otc | Type: HUMAN OTC DRUG LABEL
Date: 20220308

ACTIVE INGREDIENTS: ALCOHOL 75 mL/100 mL
INACTIVE INGREDIENTS: .ALPHA.-TOCOPHEROL ACETATE; WATER; GLYCERIN; CARBOMER INTERPOLYMER TYPE A (ALLYL SUCROSE CROSSLINKED); EDETOL; ALOE VERA LEAF

Active ingredient

Ethyl Alcohol 75%

Purpose

Antiseptic

Use

Hand Sanitizer to help reduce bacteria on the skin.

Warnings

Flammable. Keep away from fire or flame.

For external use only.

When using this product do not use in or near the eyes. In case of contact, rinse eyes thoroughly with water.

Stop use and ask a doctor if irritation or rash appears and lasts.

Keep out of reach of children

If swallowed, get medical help or contact a Posion Control Center right away.

Directions

- Put enough product in your palm to cover hands and rub hands together briskly until dry.
- Children under 6 years of age should be supervised when using this product.

Other information

Store below 104F(40C)

Inactive ingredients

AQUA ,

GLYCERIN ,

ACRYLATES/C10-30 ALKYL ACRYLATE CROSSPOLYMER,

TETRAHYDROXYPROPYL ETHYLENEDIAMINE,

ALOE BARBADENSIS LEAF EXTRACT ,

TOCOPHERYL ACETATE